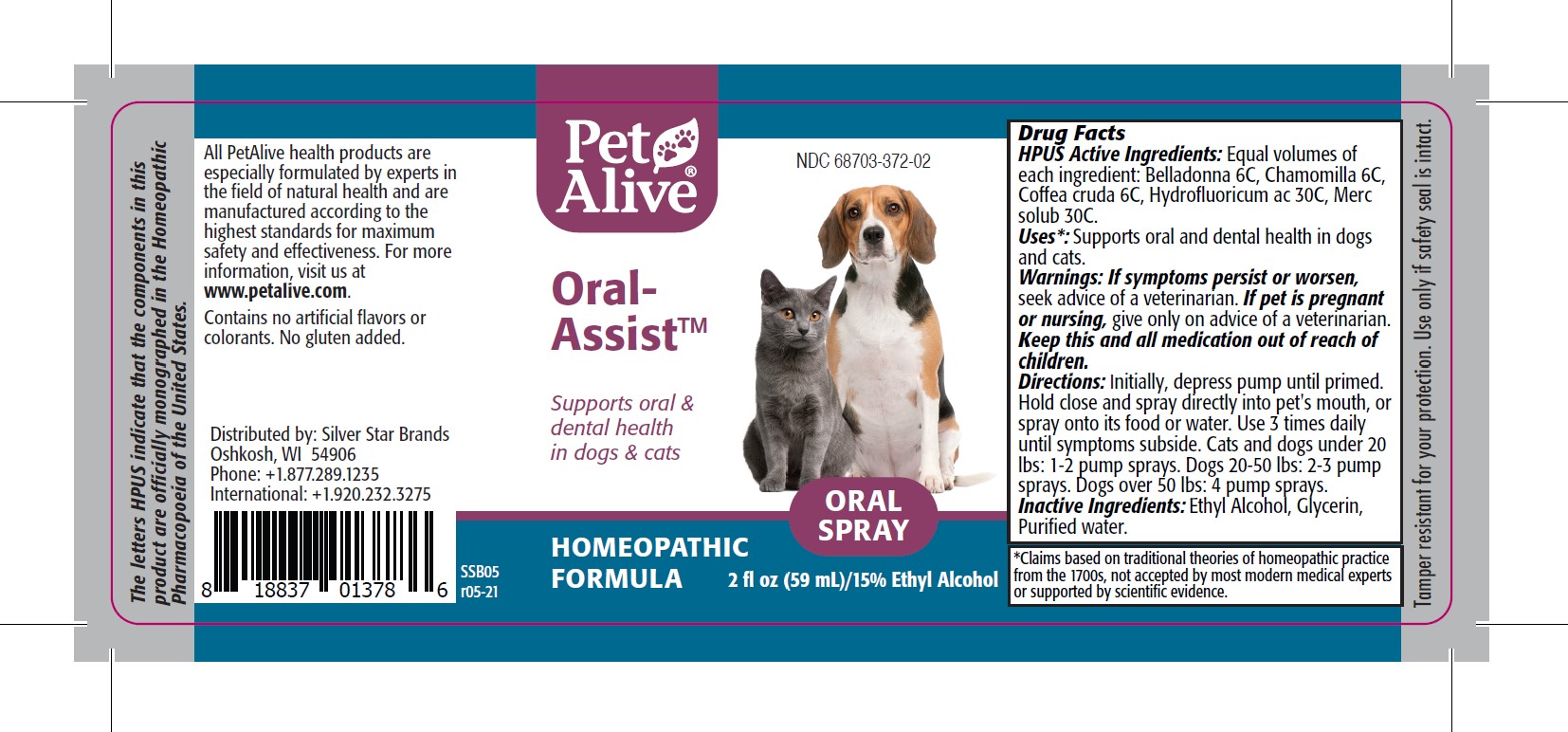 DRUG LABEL: PetAlive Oral-Assist
NDC: 68703-372 | Form: SPRAY
Manufacturer: SILVER STAR BRANDS
Category: homeopathic | Type: OTC ANIMAL DRUG LABEL
Date: 20251216

ACTIVE INGREDIENTS: ATROPA BELLADONNA 6 [hp_C]/59 mL; MATRICARIA CHAMOMILLA 6 [hp_C]/59 mL; ARABICA COFFEE BEAN 6 [hp_C]/59 mL; HYDROFLUORIC ACID 30 [hp_C]/59 mL; MERCURIUS SOLUBILIS 30 [hp_C]/59 mL
INACTIVE INGREDIENTS: ALCOHOL; glycerin; WATER

PetAlive Oral-Assist

PURPOSE

Supports oral & dental health in dogs & cats

HPUS Active Ingredients:

Belladonna 6C
Chamomilla 6C
Coffea cruda 6C
Hydrofluoricum ac 30C
Merc solub 30C

INDICATIONS AND USAGE

Uses: Supports oral and dental health in dogs and cats.

WARNINGS

Warnings: If symptoms persist or worsen, seek advice of a veterinarian

PREGNANCY OR BREAST FEEDING

If pet is pregnant or nursing, give only on advice of a veterinarian

KEEP OUT OF REACH OF CHILDREN

Keep this and all medication out of reach of children

DOSAGE AND ADMINISTRATION

Directions: Initially, depress pump until primed. Hold close and spray directly into pet's mouth, or spray onto its food or water. Use 3 times daily until symptoms subside. Cats and dogs under 20 lbs: 1-2 pump sprays. Dogs 20-50 lbs: 2-3 pump sprays. Dogs over 50 lbs: 4 pump sprays.

Inactive Ingredients: Ethyl Alcohol, Glycerin, Purified water.

INFORMATION FOR OWNERS/CAREGIVERS

The letters HPUS indicate that the components in this product are officially monographed in the Homeopathic Pharmacopoeia of the United States.

All PetAlive health products are especially formulated by experts in the field of natural health and are manufactured according to the highest standards for maximum safety and effectiveness. For more information, visit us at www.petalive.com.

Contains no artificial flavors or colorants. No gluten added.

Distributed by: Silver Star Brands
Oshkosh, WI 54906
Phone: +1.877.289.1235
International: +1.920.232.3275

STORAGE AND HANDLING

Tamper resistant for your protection. Use only if safety seal is intact